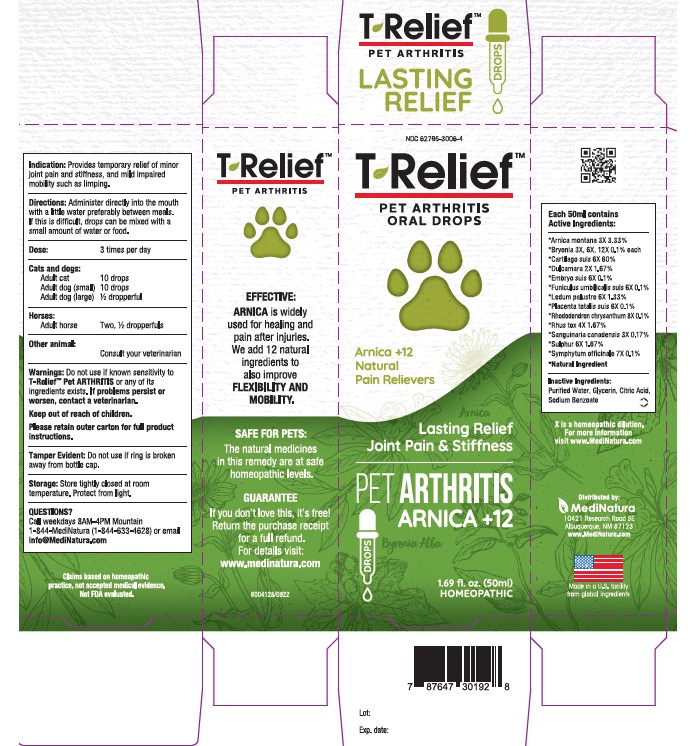 DRUG LABEL: T-Relief Pet Arthritis
NDC: 62795-3006 | Form: SOLUTION/ DROPS
Manufacturer: MediNatura New Mexico Inc
Category: homeopathic | Type: OTC ANIMAL DRUG LABEL
Date: 20230309

ACTIVE INGREDIENTS: SOLANUM DULCAMARA TOP 2 [hp_X]/50 mL; ARNICA MONTANA 3 [hp_X]/50 mL; TOXICODENDRON PUBESCENS LEAF 4 [hp_X]/50 mL; SANGUINARIA CANADENSIS ROOT 3 [hp_X]/50 mL; BRYONIA ALBA ROOT 3 [hp_X]/50 mL; SUS SCROFA CARTILAGE 6 [hp_X]/50 mL; SULFUR 6 [hp_X]/50 mL; LEDUM PALUSTRE TWIG 6 [hp_X]/50 mL; SUS SCROFA UMBILICAL CORD 6 [hp_X]/50 mL; SUS SCROFA PLACENTA 6 [hp_X]/50 mL; RHODODENDRON AUREUM LEAF 8 [hp_X]/50 mL; COMFREY ROOT 7 [hp_X]/50 mL
INACTIVE INGREDIENTS: WATER; GLYCERIN; CITRIC ACID ACETATE; Sodium Benzoate

T-Relief Pet Arthritis

Warnings:

Do not use if known sensitivity to T-Relief™ Pet ARTHRITIS
or any of its ingredients exists. If problems persist or worsen, contact a
veterinarian. Keep out of reach of children.

Indication

Provides temporary relief of minor joint pain and stiffness, and
mild impaired mobility such as limping.–

Directions

Directions: Administer directly into the mouth with a little water preferably
between meals. If this is difficult, drops can be mixed with a small amount
of water or food.–
Dose: 3 times per day – Cats & dogs: Adult cat – 10 drops. Adult dog
(small) – 10 drops. Adult dog (large) – ½ dropperful. Horses: Adult horse –
Two, ½ dropperfuls. Other animal: Consult your veterinarian.–

Inactive Ingredients:

Purified Water, Glycerin, Citric Acid, Sodium Benzoate

Keep out of reach of children.

Purpose

Provides temporary relief of minor joint pain and stiffness, and
mild impaired mobility such as limping.–

Active Ingredients:

Each 50mL contains: *Arnica montana 3X 3.33%,
*Bryonia 3X, 6X, 12X 0.1% each, *Cartilago suis 6X 60%, *Dulcamara 2X
1.67%, *Embryo suis 6X 0.1%, *Funiculus umbilicalis suis 6X 0.1%,
*Ledum palustre 6X 1.33%, *Placenta totalis suis 6X 0.1%, *Rhododendron
chrysanthum 8X 0.1%, *Rhus tox 4X 1.67%, *Sanguinaria canadensis 3X
0.17%, *Sulphur 6X 1.67%, *Symphytum officinale 7X 0.01%

PACKAGE LABEL

Add image transcription here...